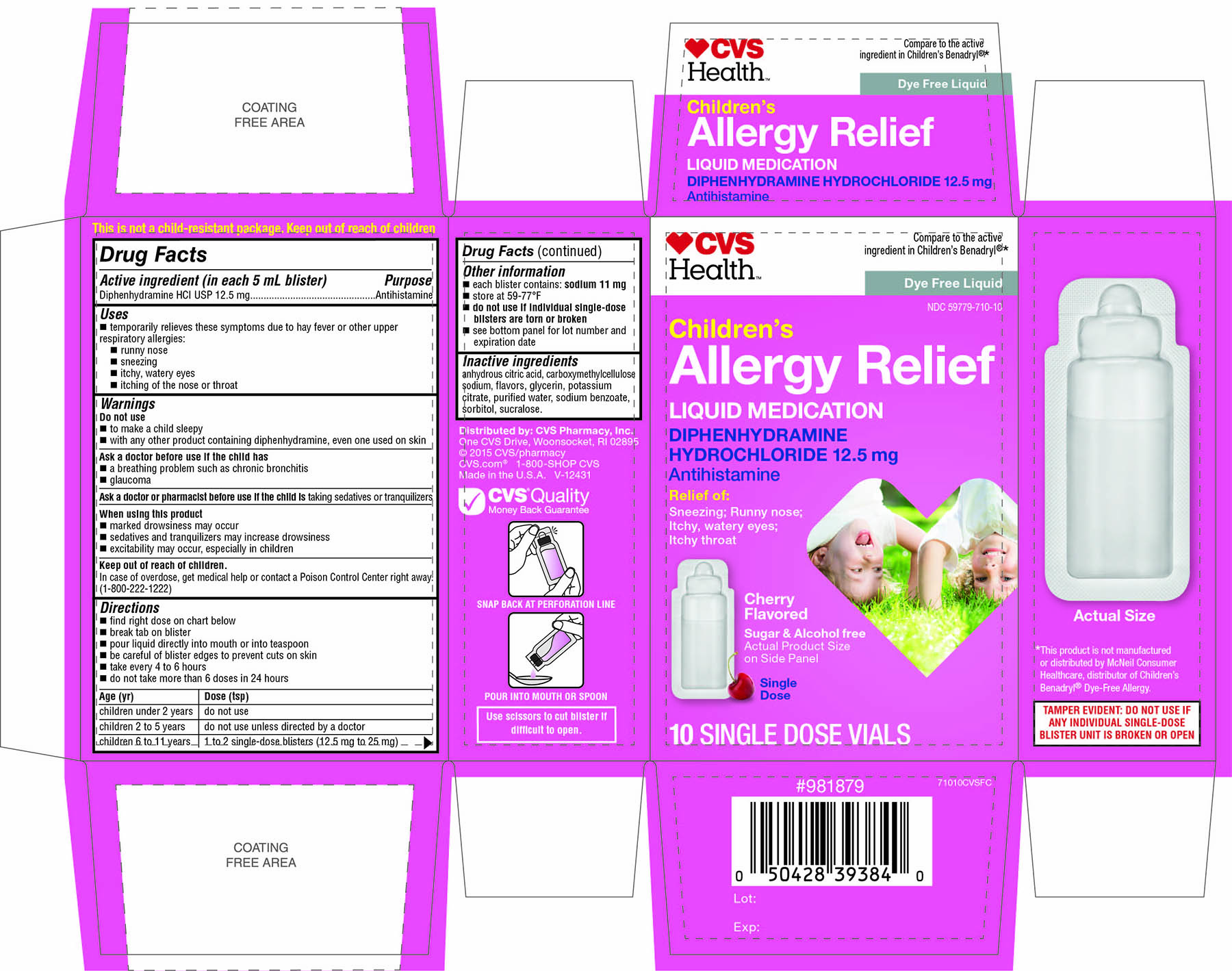 DRUG LABEL: CVS Health Childrens Allergy Relief
NDC: 59779-793 | Form: LIQUID
Manufacturer: CVS Pharmacy,Inc.
Category: otc | Type: HUMAN OTC DRUG LABEL
Date: 20171230

ACTIVE INGREDIENTS: Diphenhydramine hydrochloride 12.5 mg/5 mL
INACTIVE INGREDIENTS: anhydrous citric acid; CARBOXYMETHYLCELLULOSE SODIUM; glycerin; POTASSIUM CITRATE; water; sodium benzoate; sorbitol; SUCRALOSE

CVS Health Childrens Allergy Relief

Drug Facts

Active ingredient (in each 5 mL blister)

Diphenhydramine HCl USP 12.5 mg

Purpose

Antihistamine

Uses

- temporarily relieves these symptoms due to hay fever or other upper respiratory allergies:
  - runny nose
  - sneezing
  - itchy, watery eyes
  - itching of the nose or throat

Warnings

Do not use

- to make a child sleepy
- with any other product containing diphenhydramine, even one used on skin

Ask a doctor before use if the child has

- a breathing problem such as chronic bronchitis
- glaucoma

Ask a doctor or pharmacist before use if the child is taking sedatives or tranquilizers

When using this product

- marked drowsiness may occur
- sedatives and tranquilizers may increase drowsiness
- excitability may occur, especially in children

Keep out of reach of children.

In case of overdose, get medical help or contact a Poison Control Center right away. (1-800-222-1222)

Directions

- find right dose on chart below
- break tab on blister
- pour liquid directly into mouth or into teaspoon
- be careful of blister edges to prevent cuts on skin
- take every 4 to 6 hours
- do not take more than 6 doses in 24 hours

Age (yr) | Dose (tsp)
children under 2 years | do not use
children 2 to 5 years | do not use unless directed by a doctor
children 6 to 11 years | 1 to 2 single-dose blisters(12.5mg to 25mg)

Other information

- each blister contains: sodium 11 mg
- store at (59-77°F)
- do not use if individual single-dose blisters are torn or broken
- see bottom panel for lot number and expiration date

Inactive ingredients

anhydrous citric acid, carboxymethylcellulose sodium, flavors, glycerin, potassium citrate, purified water, sodium benzoate, sorbitol, sucralose.

PRINCIPAL DISPLAY PANEL

CVS Health ™

Compare to the active ingredient in Children's
Benadryl® *

Dye-Free Liquid

Children’s Allergy Relief

Liquid Medication

DIPHENHYDRAMINE HYDROCHLORIDE 12.5 mg

Antihistamine

alcohol and sugar free

Relief of:

Sneezing;
runny nose;
itchy, watery eyes;
itchy throat

Cherry Flavored

Sugar & Alcohol free

Actual Product size on Side Panel

Single Dose

10 SINGLE DOSE VIALS

This is not a child-resistant package. Keep out of reach of children

*This product is not manufactured or distributed by McNeil Consumer Healthcare, distributor of Children’s Benadryl® Dye –Free Allergy.

TAMPER EVIDENT: DO NOT USE IF ANY INDIVIDUAL SINGLE-DOSE BLISTER UNIT IS BROKEN OR OPEN

Distributed by: CVS Pharmacy, Inc.

One CVS Drive,Woonsocket, RI 02895

© 2015CVS/pharmacy

CVS.com® 1-800-SHOP CVS

Made in the U.S.A.

V-12431

CVS Quality

Money Back Guarantee

SNAP BACK AT PERFORATION LINE

POUR INTO MOUTH OR SPOON

Use scissors to cut blister if difficult to open.